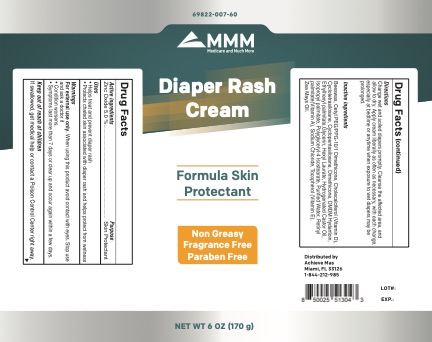 DRUG LABEL: MMM Diaper Rash Cream
NDC: 69822-007 | Form: CREAM
Manufacturer: Southern Sales & Services, Inc.
Category: otc | Type: HUMAN OTC DRUG LABEL
Date: 20210101

ACTIVE INGREDIENTS: ZINC OXIDE 5 g/100 g
INACTIVE INGREDIENTS: CHOLECALCIFEROL; HYDROGENATED CASTOR OIL; DIMETHICONE; TOCOPHEROL; HEXYL LAURATE; DIMETHICONE CROSSPOLYMER (450000 MPA.S AT 12% IN CYCLOPENTASILOXANE); ISOPROPYL PALMITATE; WATER; VITAMIN A PALMITATE; GLYCERIN; MONOPHENYLHEPTAMETHYLCYCLOTETRASILOXANE; POLYGLYCERYL-4 ISOSTEARATE; CETYL PEG/PPG-10/1 DIMETHICONE (HLB 1.5); SODIUM CHLORIDE; YELLOW WAX; DMDM HYDANTOIN; ETHYLHEXYL PALMITATE

MMM Diaper Rash Cream

Active Ingredients Purpose

Zinc Oxide 5% Skin Protectant

PURPOSE

• Helps treat and prevent diaper rash.

• Protects chafed skin associated with diaper rash and helps protect from wetness.

WARNINGS

For external use only. When using this product avoid contact with eyes. Stop use and ask a doctor if

- Condition worsens.
- Symptoms last more than 7 days or clear up and occur again within a few days.

If swallowed, get medical help or contact a Poison Control Center right away.

INDICATIONS AND USAGE

Change wet and soiled diapers promptly. Cleanse the affected area, and allow to dry. Apply cream liberally as often as necessary, with each change, especially at bedtime or anytime when exposure to wet diapers may be prolonged.

Stop use and ask a doctor if

• Condition worsens.
• Symptoms last more than 7 days or clear up and occur again within a few days.

DOSAGE AND ADMINISTRATION

Change wet and soiled diapers promptly. Cleanse the affected area, and allow to dry. Apply cream liberally as often as necessary, with each change, especially at bedtime or anytime when exposure to wet diapers may be prolonged.

INACTIVE INGREDIENT

Purified Water, cyclotetrasiloxane , Isopropyl palmitate, Ethylhexyl palmitate, Glycerin, Cyclopentasiloxane, Polyglyceryl-4 Isostearate, Cetyl PEG/PPG-10/1 Dimethicone, Hexyl Laurate, Dimethicone, Tocopherol (Vitamin E), Zea Mays Oil, Retinyl palmitate(Vitamin A), Cholecalciferol (Vitamin D), Beeswax, Hydrogenated Castor Oil, Sodium Chloride, DMDM Hydantoin.

KEEP OUT OF REACH OF CHILDREN

If swallowed, get medical help or contact a Poison Control Center right away